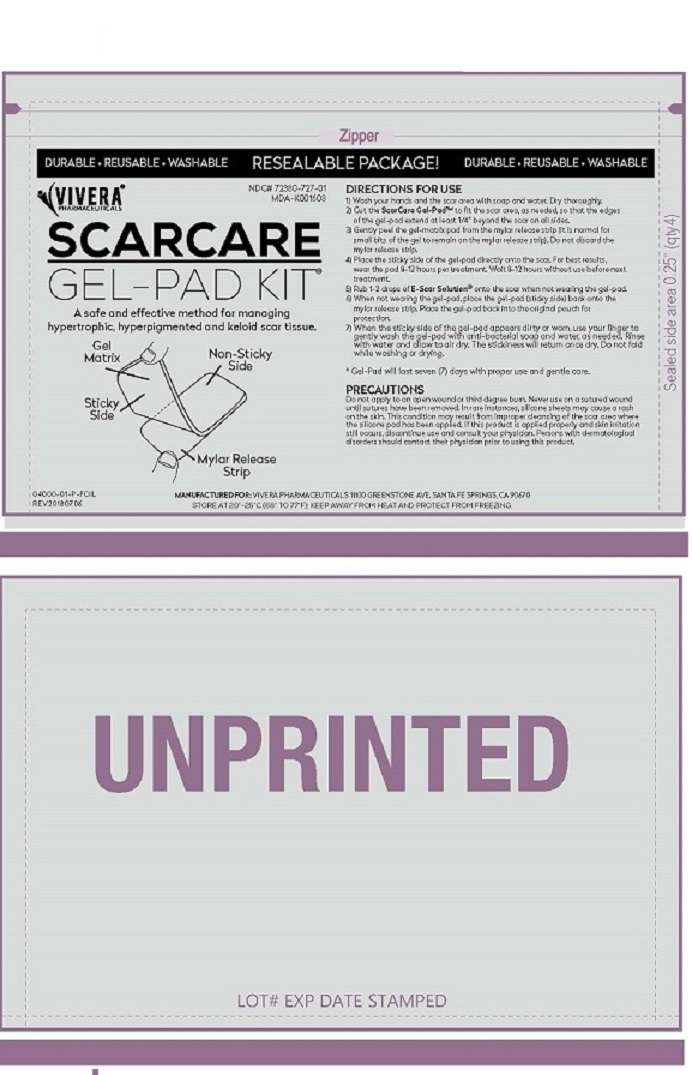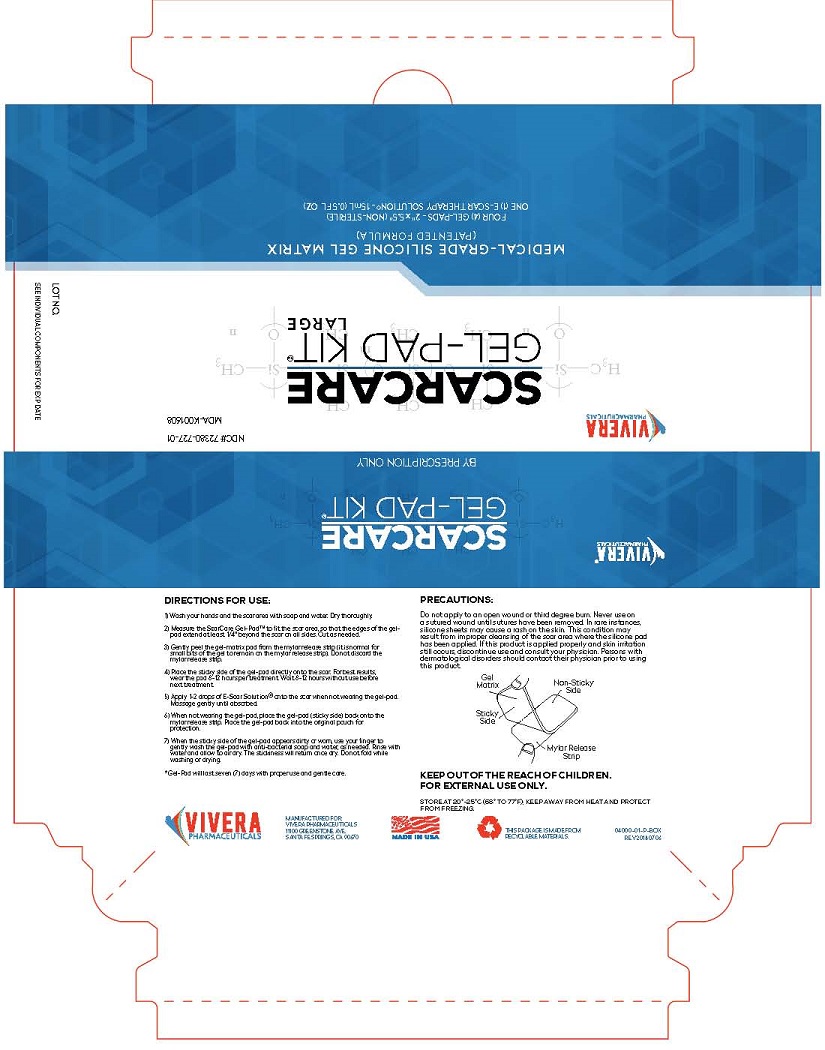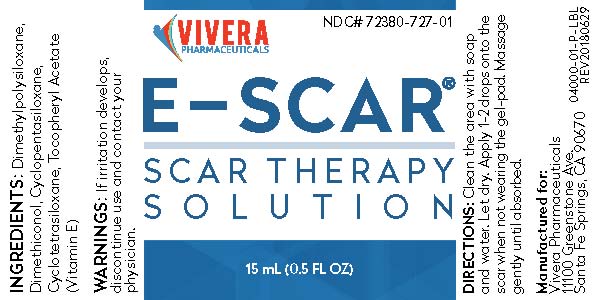 DRUG LABEL: VIVERA SCARCARE PATCH WITH E-SCAR
NDC: 72380-183 | Form: KIT | Route: TOPICAL
Manufacturer: Vivera Pharmaceuticals, Inc.
Category: other | Type: MEDICAL DEVICE
Date: 20190301
INACTIVE INGREDIENTS: DIMETHICONE 3 mL/15 mL; DIMETHICONOL (40 CST) 3 mg/15 mL; CYCLOMETHICONE 5 3 mg/15 mL; CYCLOMETHICONE 4 3 mg/15 mL; .ALPHA.-TOCOPHEROL ACETATE 3 mg/15 mL

VIVERA SCARCARE PATCH WITH E-SCAR

INDICATIONS AND USAGE

DIRECTIONS FOR USE:

1) Wash hands and the scar area with soap and water. Dry thoroughly.

2) Cut the ScarCare Gel-PadTM to fit the scar area, as needed, so that the edges

of the gel-pad extend at least 1/4" beyond the edge of the scar on all sides.

3) Gently peel the gel-matrix pad from the mylar release strip. It is normal for

small bits of the gel to remain on the mylar release strip. Do not discard the

mylar release strip.

4) Place the sticky side of the gel-pad directly onto the scar. For best results,

wear the pad 8-12 hours per teatment. Wait 8-12 hours without use before next

treatment.

5) Rub 1-2 drops of E-Scar Solution onto the scar when not wearing the gel-pad.

6) When not wearing the gel-pad, place the gel-pad (sticky side) back onto the

mylar release strip. Place the gel-pad back into the original pouch for

protection.

7) When the sticky side of the gel-pad appears dirty or worn, use your finger to

gently wash the gel-pad with antibacterial soapand water, as needed. Rinse with

water and allow to air dry. The stickiness will return once dry. Do not fold while

washing or drying.

* Gel-pad will last seven (7) days with proper use and gentle care.

DIRECTIONS: Clean the area with soap

and water. Let dry. Apply 1-2 drops onto the

scar when not wearing the gel-pad. Massage

gently until absorbed.

WARNINGS: If irritation develops,

discontinue use and contact your physician.

PRECAUTIONS:

Do not apply to open wound or third degree burn. Never use on

a sutured wound until the sutures have been removed. In rare instances,

silicone sheets may cause a rash on the skin. This condition may

result from improper cleansing of the scar area where the silicone pad

has been applied. If this product has been applied properly and skin irritation

still occurs, discontinue use and consult your physician. Persons with

dermatological disorders should contact their physician prior to using

this product.

KEEP OUT OF REACH OF CHILDREN.

FOR EXTERNAl USE ONLY.

INACTIVE INGREDIENT

INGREDIENTS: Dimethylpolysiloxane,

Dimethiconol, Cyclopentasiloxane,

Cyclotetrasiloxane, Tocopheryl Acetate,

(Vitamin E)

Principal Display Package

VIVERA

PHARMACEUTICALS

SCARCARE

GEL-PAK KIT

BY PRESCRIPTION ONLY

VIVERA NDC #72380-727-01

PHARMACEUTICALS MDA K001608

LOT NO.

SEE INDIVIDUAL COMPONENTS FOR EXP DATE

MEDICAL-GRADE SILICONE GEL MATRIX

(PATENTED FORMULA)

FOUR (4) GEL-PADS - 2" X 5.5" (NON-STERILE)

ONE (1) E-SCAR THERAPY SOLUTION - 15 mL (0.5 FL OZ)

DIRECTIONS FOR USE:

1) Wash hands and the scar area with soap and water. Dry thoroughly.

2) Cut the ScarCare Gel-PadTM to fit the scar area, as needed, so that the edges

of the gel-pad extend at least 1/4" beyond the edge of the scar on all sides.

3) Gently peel the gel-matrix pad from the mylar release strip. It is normal for

small bits of the gel to remain on the mylar release strip. Do not discard the

mylar release strip.

4) Place the sticky side of the gel-pad directly onto the scar. For best results,

wear the pad 8-12 hours per teatment. Wait 8-12 hours without use before next

treatment.

5) Rub 1-2 drops of E-Scar Solution onto the scar when not wearing the gel-pad.

6) When not wearing the gel-pad, place the gel-pad (sticky side) back onto the

mylar release strip. Place the gel-pad back into the original pouch for

protection.

7) When the sticky side of the gel-pad appears dirty or worn, use your finger to

gently wash the gel-pad with antibacterial soapand water, as needed. Rinse with

water and allow to air dry. The stickiness will return once dry. Do not fold while

washing or drying.

* Gel-pad will last seven (7) days with proper use and gentle care.

PRECAUTIONS:

Do not apply to open wound or third degree burn. Never use on

a sutured wound until the sutures have been removed. in rare instances,

silicone sheets may cause a rash on the skin. This condition may

result from improper cleansing of the scar area where the silicone pad

has been applied. If this product has been applied properly and skin irritation

still occurs, discontinue use and consult your physician. Persons with

dermatological disorders should contact their physician prior to using

this product.

KEEP OUT OF REACH OF CHILDREN.

FOR EXTERNAl USE ONLY.

STORE AT 20O-25O C (68O TO 77O F) KEEP AWAY FRO HEAT AND PROTECT FROM FREEZING

VIVERA

PHARMACEUTICALS

MANUFACTURED FOR:

VIVERA PHARMACEUTICALS

11100 GREENSTONE AVE.

SANTA FE SPRINGS, CA 90670

04000-01-P-BOX

REV 20180706

res

PACKAGE LABEL

VIVERA NDC# 72380-727-01

PHARMACEUTICALS

E-SCAR

SCAR THERAPY

SOLUTION

15 mL (0.5 FL OZ)

INGREDIENTS: Dimethylpolysiloxane,

Dimethiconol, Cyclopentasiloxane,

Cyclotetrasiloxane, Tocopheryl Acetate,

(Vitamin E)

WARNINGS: If irritation develops,

discontinue use and contact your physician.

DIRECTIONS: Clean the area with soap

and water. Let dry. Apply 1-2 drops onto the

scar when not wearing the gel-pad. Massage

gently until absorbed.

Manufactured for:

Vivera Pharmaceuticals

11100 Greenstone Ave. 04000-01-PL-LBL

Santa Fe Springs, CA 90670 REV20180629

ZIPPER

DURABLE ● REUSABLE ● WASHABLE RESEALABLE PACKAGE! DURABLE ● REUSABLE ● WASHABLE

VIVERA NDC# 72380-727-01

PHARMACEUTICALS MDA-K001608

SCARCARE

GEL-PAD KIT

A safe and effective method for managing

hypertrophic, hyperpigmented and keloid scar tissue.

DIRECTIONS FOR USE:

1) Wash hands and the scar area with soap and water. Dry thoroughly.

2) Cut the ScarCare Gel-PadTM to fit the scar area, as needed, so that the edges

of the gel-pad extend at least 1/4" beyond the edge of the scar on all sides.

3) Gently peel the gel-matrix pad from the mylar release strip. It is normal for

small bits of the gel to remain on the mylar release strip. Do not discard the

mylar release strip.

4) Place the sticky side of the gel-pad directly onto the scar. For best results,

wear the pad 8-12 hours per teatment. Wait 8-12 hours without use before next

treatment.

5) Rub 1-2 drops of E-Scar Solution onto the scar when not wearing the gel-pad.

6) When not wearing the gel-pad, place the gel-pad (sticky side) back onto the

mylar release strip. Place the gel-pad back into the original pouch for

protection.

7) When the sticky side of the gel-pad appears dirty or worn, use your finger to

gently wash the gel-pad with antibacterial soapand water, as needed. Rinse with

water and allow to air dry. The stickiness will return once dry. Do not fold while

washing or drying.

* Gel-pad will last seven (7) days with proper use and gentle care.

PRECAUTIONS:

Do not apply to open wound or third degree burn. Never use on

a sutured wound until the sutures have been removed. in rare instances,

silicone sheets may cause a rash on the skin. This condition may

result from improper cleansing of the scar area where the silicone pad

has been applied. If this product has been applied properly and skin irritation

still occurs, discontinue use and consult your physician. Persons with

dermatological disorders should contact their physician prior to using

this product.

MANUFACTURED FOR VIVERA PHARMACEUTICALS, 11100 GREENSTONE AVE., SANTA FE SPRINGS, CA 90670

STORE AT 20O-25O C (68O TO 77O F) KEEP AWAY FRO HEAT AND PROTECT FROM FREEZING

KEEP OUT OF REACH OF CHILDREN.

FOR EXTERNAL USE ONLY.

04000-01-P-FOL

REV20180706

UNPRINTED

LOT # EXP DATE STAMPED

res